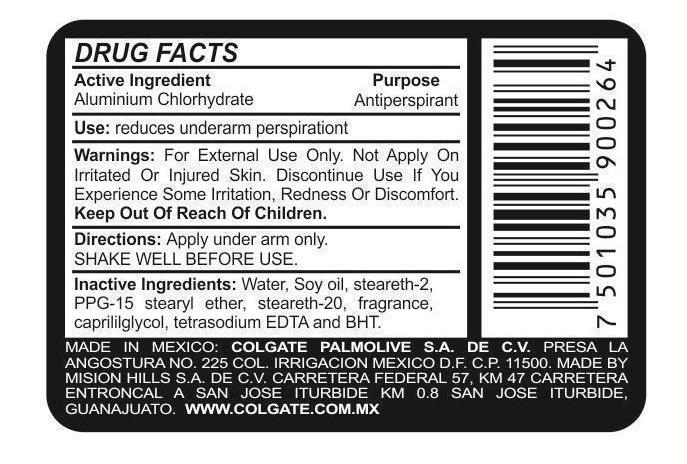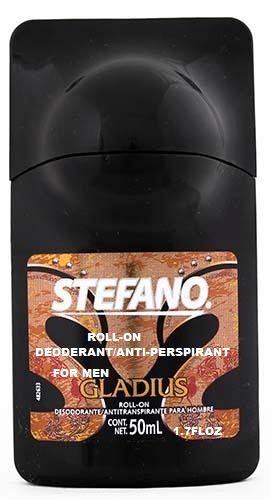 DRUG LABEL: Stefano Gladius
NDC: 69772-040 | Form: LIQUID
Manufacturer: Teresa Cecena DBA Genesis
Category: otc | Type: HUMAN OTC DRUG LABEL
Date: 20150602

ACTIVE INGREDIENTS: ALUMINUM CHLOROHYDRATE 25 g/100 mL
INACTIVE INGREDIENTS: EDETATE SODIUM; BUTYLATED HYDROXYTOLUENE; WATER; STEARETH-2; PPG-15 STEARYL ETHER; ISOSTEARETH-20; CAPRYLYL GLYCOL

ACTIVE INGREDIENT

Aluminum Chlorohydrate

Purpose:

Antiperspirant

KEEP OUT OF THE REACH OF CHILDREN

USE:

Reduces underarm persperation

WARNINGS

FOR EXTERNAL USE ONLY

DIRECTIONS

APPLY UNDER ARM ONLY

SHAKE WELL BEFORE USE

WARNINGS AND PRECAUTIONS

DO NOT APPLY ON IRRITATED OR INJURED SKIN. DISCONTINUE USE IF YOU EXPERIENCE SOME IRRITATION, REDNESS OR DISCOMFORT

INACTIVE INGREDIENT

WATER, SOYOIL, STEARTH-2, PPG-15 STEARYL ETHER, STEARETH-20, FRAGANCE, CAPRYLY GLYCOL. TETRASOSIUM EDTA, AND BHT